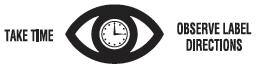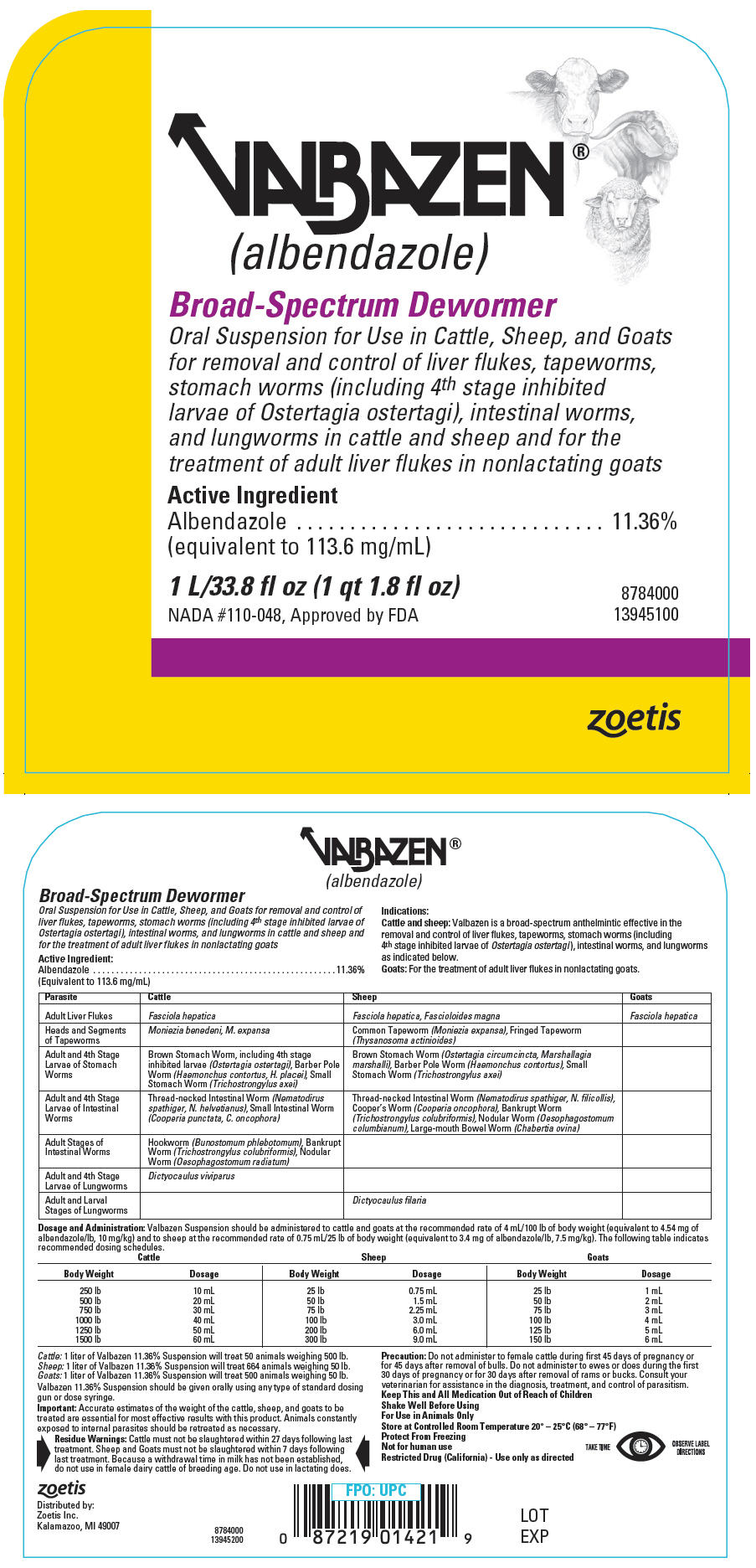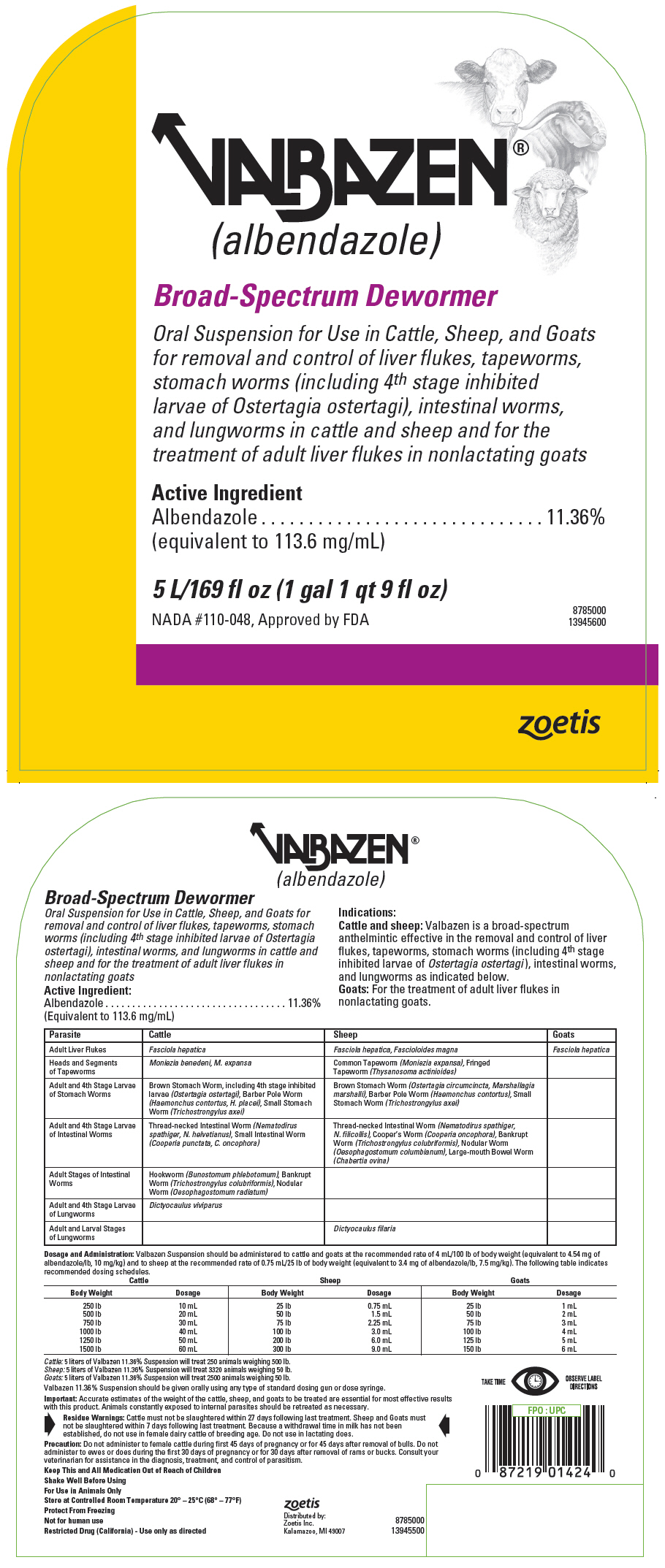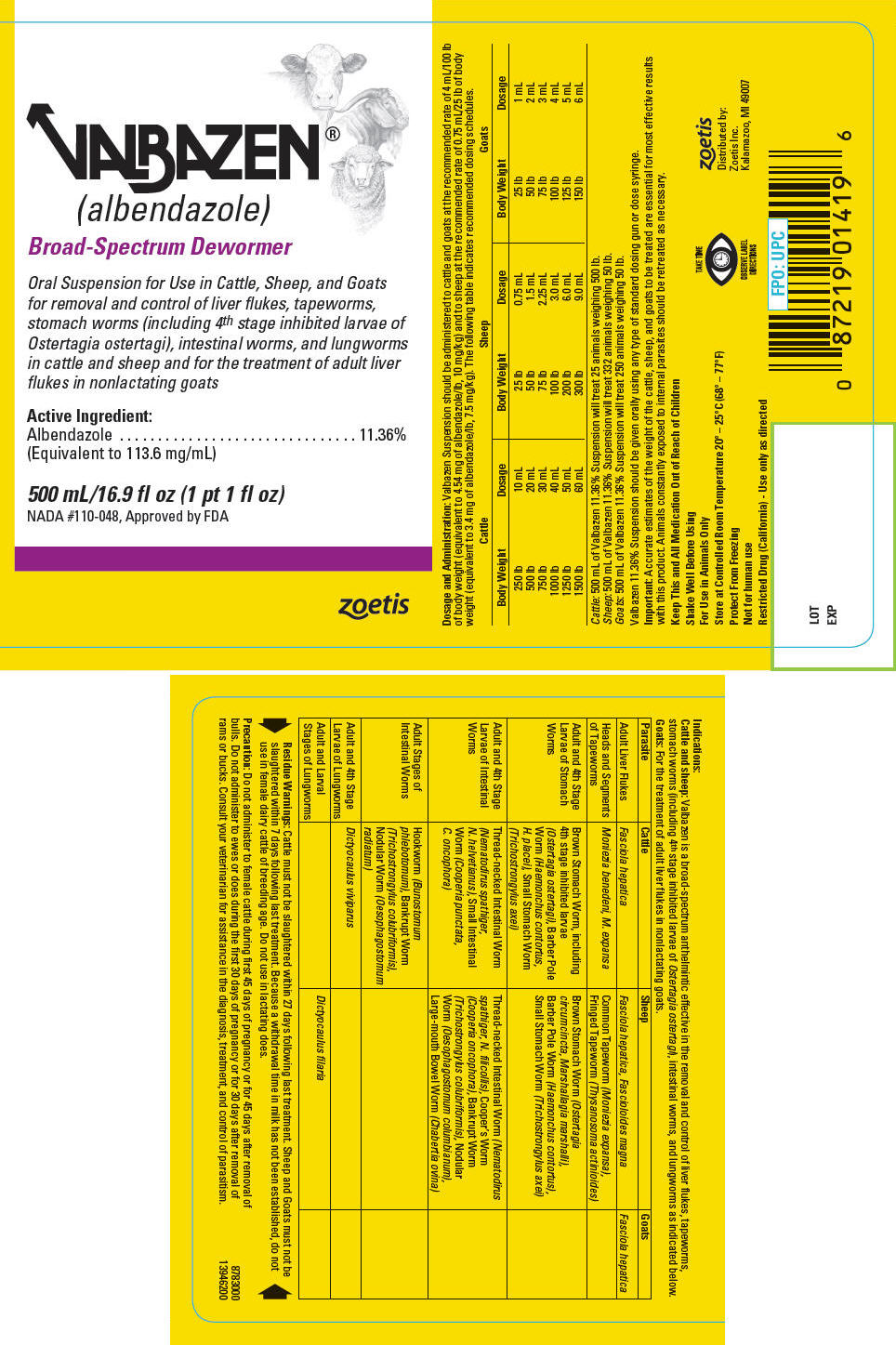 DRUG LABEL: Valbazen
NDC: 54771-8783 | Form: SUSPENSION
Manufacturer: Zoetis Inc.
Category: animal | Type: OTC ANIMAL DRUG LABEL
Date: 20200626

ACTIVE INGREDIENTS: albendazole 113.6 mg/1 mL
INACTIVE INGREDIENTS: CARBOXYMETHYLCELLULOSE SODIUM 6 mg/1 mL; GLYCERIN; POTASSIUM SORBATE; POLYSORBATE 80; BENZOIC ACID

VALBAZEN®

DESCRIPTION

VALBAZEN®
(albendazole oral suspension)

Broad-Spectrum Dewormer

Oral Suspension for Use in Cattle, Sheep, and Goats for removal and control of liver flukes, tapeworms, stomach worms (including 4th stage inhibited larvae of Ostertagia ostertagi), intestinal worms, and lungworms in cattle and sheep and for the treatment of adult liver flukes in nonlactating goats.

Active Ingredient:
Albendazole (Equivalent to 113.6 mg/mL) | 11.36%

Approved by FDA under NADA # 110-048

Indications

Cattle and sheep: Valbazen is a broad-spectrum anthelmintic effective in the removal and control of liver flukes, tapeworms, stomach worms (including 4th stage inhibited larvae of Ostertagia ostertagi), intestinal worms, and lungworms as indicated below.

Goats: For the treatment of adult liver flukes in nonlactating goats.

Parasite | Cattle | Sheep | Goats
Adult Liver Flukes | Fasciola hepatica | Fasciola hepatica, Fascioloides magna | Fasciola hepatica
Heads and Segments of Tapeworms | Moniezia benedeni, M. expansa | Common Tapeworm (Moniezia expansa), Fringed Tapeworm (Thysanosoma actinioides)
Adult and 4th Stage Larvae of Stomach Worms | Brown Stomach Worm, including 4th stage inhibited larvae (Ostertagia ostertagi), Barber Pole Worm (Haemonchus contortus, H. placei), Small Stomach Worm (Trichostrongylus axei) | Brown Stomach Worm (Ostertagia circumcincta, Marshallagia marshalli), Barber Pole Worm (Haemonchus contortus), Small Stomach Worm (Trichostrongylus axei)
Adult and 4th Stage Larvae of Intestinal Worms | Thread-necked Intestinal Worm (Nematodirus spathiger, N. helvetianus), Small Intestinal Worm (Cooperia punctata, C. oncophora) | Thread-necked Intestinal Worm (Nematodirus spathiger, N. filicollis), Cooper's Worm (Cooperia oncophora), Bankrupt Worm (Trichostrongylus colubriformis), Nodular Worm (Oesophagostomum columbianum), Large-mouth Bowel Worm (Chabertia ovina)
Adult Stages of Intestinal Worms | Hookworm (Bunostomum phlebotomum), Bankrupt Worm (Trichostrongylus colubriformis), Nodular Worm (Oesophagostomum radiatum)
Adult and 4th Stage Larvae of Lungworms | Dictyocaulus viviparus
Adult and Larval Stages of Lungworms |  | Dictyocaulus filaria

Dosage and Administration

Valbazen Suspension should be administered to cattle and goats at the recommended rate of 4 mL/100 lb of body weight (equivalent to 4.54 mg of albendazole/lb, 10 mg/kg) and to sheep at the recommended rate of 0.75 mL/25 lb of body weight (equivalent to 3.4 mg of albendazole/lb, 7.5 mg/kg). The following table indicates recommended dosing schedules. Do not underdose. Ensure each animal receives a complete dose based on a current body weight. Underdosing may result in ineffective treatment, and encourage the development of parasite resistance.

Cattle |  | Sheep |  | Goats
Body Weight | Dosage | Body Weight | Dosage | Body Weight | Dosage
250 lb | 10 mL | 25 lb | 0.75 mL | 25 lb | 1 mL
500 lb | 20 mL | 50 lb | 1.5 mL | 50 lb | 2 mL
750 lb | 30 mL | 75 lb | 2.25 mL | 75 lb | 3 mL
1000 lb | 40 mL | 100 lb | 3.0 mL | 100 lb | 4 mL
1250 lb | 50 mL | 200 lb | 6.0 mL | 125 lb | 5 mL
1500 lb | 60 mL | 300 lb | 9.0 mL | 150 lb | 6 mL

Cattle: 1 liter of Valbazen 11.36% Suspension will treat 50 animals weighing 500 lb.

Sheep: 1 liter of Valbazen 11.36% Suspension will treat 664 animals weighing 50 lb.

Goats: 1 liter of Valbazen 11.36% Suspension will treat 500 animals weighing 50 lb.

Valbazen 11.36% Suspension should be given orally using any type of standard dosing gun or dose syringe.

Important

Accurate estimates of the weight of the cattle, sheep, and goats to be treated are essential for most effective results with this product. Animals constantly exposed to internal parasites should be retreated as necessary.

Residue Warnings

Cattle must not be slaughtered within 27 days following last treatment. Sheep and Goats must not be slaughtered within 7 days following last treatment. Because a withdrawal time in milk has not been established, do not use in female dairy cattle of breeding age. Do not use in lactating does.

Other Warnings

Parasite resistance may develop to any dewormer, and has been reported for most classes of dewormers. Treatment with a dewormer used in conjunction with parasite management practices appropriate to the geographic area and the animal(s) to be treated may slow the development of parasite resistance. Fecal examinations or other diagnostic tests and parasite management history should be used to determine if the product is appropriate for the herd/flock, prior to the use of any dewormer. Following the use of any dewormer, effectiveness of treatment should be monitored (for example, with the use of a fecal egg count reduction test or another appropriate method). A decrease in a drug’s effectiveness over time as calculated by fecal egg count reduction tests may indicate the development of resistance to the dewormer administered. Your parasite management plan should be adjusted accordingly based on regular monitoring.

Precaution

Do not administer to female cattle during first 45 days of pregnancy or for 45 days after removal of bulls. Do not administer to ewes or does during the first 30 days of pregnancy or for 30 days after removal of rams or bucks. Consult your veterinarian for assistance in the diagnosis, treatment, and control of parasitism.

Keep This and All Medication Out of Reach of Children

Shake Well Before Using

For Use in Animals Only

STORAGE AND HANDLING

Store at Controlled Room Temperature 20° – 25°C (68° – 77°F)

Protect From Freezing

Not for human use

Restricted Drug (California) - Use only as directed

Distributed by:
Zoetis Inc.
Kalamazoo, MI 49007

40029176

LOT
EXP

PRINCIPAL DISPLAY PANEL - 1 L/33.8 fl oz Bottle Label

VALBAZEN®
(albendazole)

Broad-Spectrum Dewormer

Oral Suspension for Use in Cattle, Sheep, and Goats
for removal and control of liver flukes, tapeworms,
stomach worms (including 4th stage inhibited
larvae of Ostertagia ostertagi), intestinal worms,
and lungworms in cattle and sheep and for the
treatment of adult liver flukes in nonlactating goats

Active Ingredient
Albendazole
(equivalent to 113.6 mg/mL)
11.36%

1 L/33.8 fl oz (1 qt 1.8 fl oz)

NADA #110-048, Approved by FDA

8784000
13945100

zoetis

PRINCIPAL DISPLAY PANEL - 5 L/169 fl oz Bottle Label

VALBAZEN®
(albendazole)

Broad-Spectrum Dewormer

Oral Suspension for Use in Cattle, Sheep, and Goats
for removal and control of liver flukes, tapeworms,
stomach worms (including 4th stage inhibited
larvae of Ostertagia ostertagi), intestinal worms,
and lungworms in cattle and sheep and for the
treatment of adult liver flukes in nonlactating goats

Active Ingredient
Albendazole
(equivalent to 113.6 mg/mL)
11.36%

5 L/169 fl oz (1 gal 1 qt 9 fl oz)

NADA #110-048, Approved by FDA

8785000
13945600

zoetis

PRINCIPAL DISPLAY PANEL - 500 mL/16.9 fl oz Bottle Label

VALBAZEN®
(albendazole)

Broad-Spectrum Dewormer

Oral Suspension for Use in Cattle, Sheep, and Goats
for removal and control of liver flukes, tapeworms,
stomach worms (including 4th stage inhibited larvae of
Ostertagia ostertagi), intestinal worms, and lungworms
in cattle and sheep and for the treatment of adult liver
flukes in nonlactating goats

Active Ingredient:
Albendazole
(Equivalent to 113.6 mg/mL)
11.36%

500 mL/16.9 fl oz (1 pt 1 fl oz)

NADA #110-048, Approved by FDA

zoetis